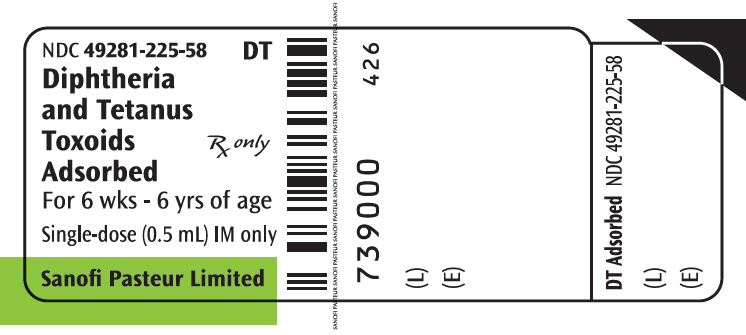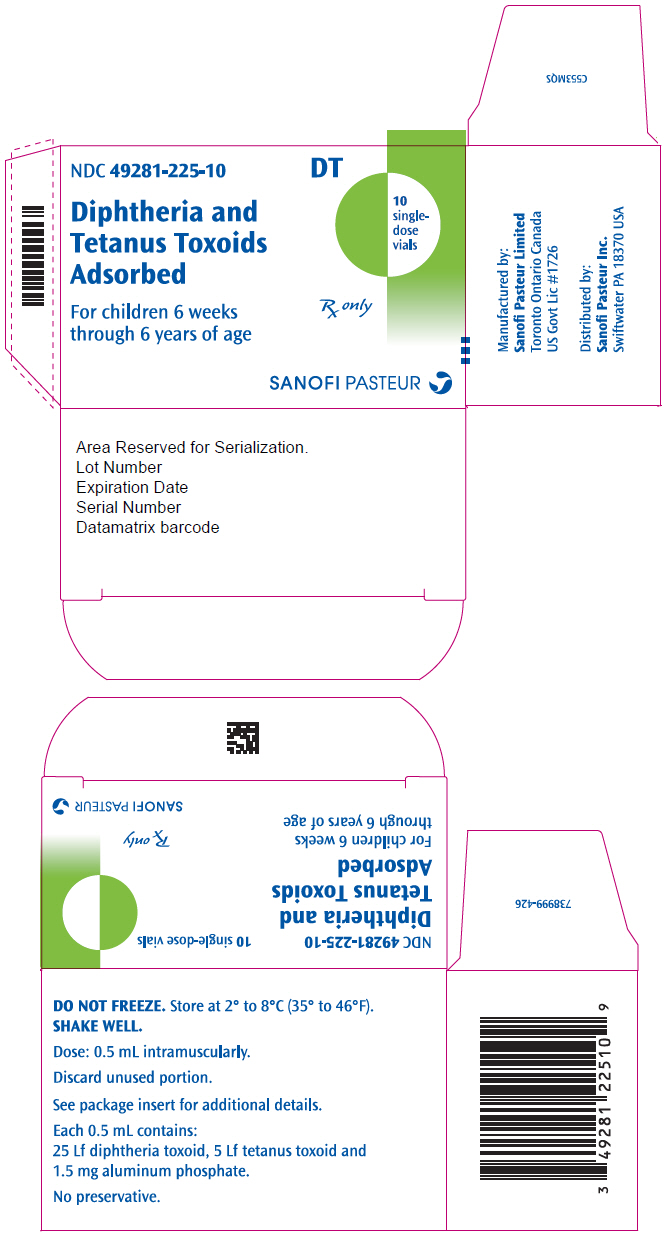 DRUG LABEL: DIPHTHERIA AND TETANUS TOXOIDS ADSORBED
NDC: 49281-225 | Form: INJECTION, SUSPENSION
Manufacturer: Sanofi Pasteur Inc.
Category: other | Type: VACCINE LABEL
Date: 20190419

ACTIVE INGREDIENTS: CORYNEBACTERIUM DIPHTHERIAE TOXOID ANTIGEN (FORMALDEHYDE INACTIVATED) 25 [Lf]/0.5 mL; CLOSTRIDIUM TETANI TOXOID ANTIGEN (FORMALDEHYDE INACTIVATED) 5 [Lf]/0.5 mL
INACTIVE INGREDIENTS: ALUMINUM PHOSPHATE 1.5 mg/0.5 mL; FORMALDEHYDE 100 ug/0.5 mL

HIGHLIGHTS OF PRESCRIBING INFORMATION

These highlights do not include all the information needed to use Diphtheria and Tetanus Toxoids Adsorbed safely and effectively. See full prescribing information for Diphtheria and Tetanus Toxoids Adsorbed.
Diphtheria and Tetanus Toxoids Adsorbed
Suspension for Intramuscular Injection
Initial U.S. Approval: 1997

1 INDICATIONS AND USAGE

Diphtheria and Tetanus Toxoids Adsorbed is a vaccine indicated for active immunization against diphtheria and tetanus. Diphtheria and Tetanus Toxoids Adsorbed is approved for use in children from 6 weeks through 6 years of age (prior to 7th birthday). (1)

2 DOSAGE AND ADMINISTRATION

The five dose immunization series consists of an injection administered at 2, 4, 6, 15-18 months and between 4 and 6 years of age. (2.1)

3 DOSAGE FORMS AND STRENGTHS

Suspension for injection, supplied in single-dose (0.5 mL) vials (3)

4 CONTRAINDICATIONS

Severe allergic reaction (e.g., anaphylaxis) after a previous dose of Diphtheria and Tetanus Toxoids Adsorbed or any other diphtheria toxoid or tetanus toxoid-containing vaccine, or any other component of this vaccine. (4)

5 WARNINGS AND PRECAUTIONS

- If Guillain-Barré syndrome occurred within 6 weeks of receipt of prior vaccine containing tetanus toxoid, the risk for Guillain-Barré syndrome may be increased following Diphtheria and Tetanus Toxoids Adsorbed vaccine. (5.2)
- Apnea following intramuscular vaccination has been observed in some infants born prematurely. The decision about when to administer an intramuscular vaccine, including Diphtheria and Tetanus Toxoids Adsorbed, to an infant born prematurely should be based on consideration of the individual infant's medical status and the potential benefits and possible risks of vaccination. (5.5)
- Syncope (fainting) has been reported following vaccination with Diphtheria and Tetanus Toxoids Adsorbed vaccine. Procedures should be in place to prevent falling injury and manage syncopal reactions. (5.6)

6 ADVERSE REACTIONS

The most common adverse reactions (≥5%) were crying, fever, and loss of appetite. (6.1)

To report SUSPECTED ADVERSE REACTIONS, contact Sanofi Pasteur Inc., at 1-800-822-2463 (1-800-VACCINE) or VAERS at 1-800-822-7967 and http://vaers.hhs.gov.

7 DRUG INTERACTIONS

Immunosuppressive therapies may reduce the response to Diphtheria and Tetanus Toxoids Adsorbed. (7.3)

FULL PRESCRIBING INFORMATION

1 INDICATIONS AND USAGE

Diphtheria and Tetanus Toxoids Adsorbed is a vaccine indicated for active immunization against diphtheria and tetanus. Diphtheria and Tetanus Toxoids Adsorbed is approved for use in children from 6 weeks through 6 years of age (prior to 7th birthday).

Diphtheria and Tetanus Toxoids and Acellular Pertussis Vaccine (DTaP) or a DTaP-containing vaccine is recommended for immunization of infants and children 6 weeks through 6 years of age. Diphtheria and Tetanus Toxoids Adsorbed should be used in instances where the pertussis vaccine component is contraindicated.

Diphtheria and Tetanus Toxoids Adsorbed is not to be used for treatment of diphtheria or tetanus infection.

2 DOSAGE AND ADMINISTRATION

For intramuscular use only.

2.1 Dosage and Schedule

Diphtheria and Tetanus Toxoids Adsorbed is approved for administration as a 5 dose series at 2, 4, 6, 15-18 months, and 4-6 years. The first dose of Diphtheria and Tetanus Toxoids Adsorbed may be administered as early as 6 weeks of age.

2.2 Administration

Parenteral drug products should be inspected visually for particulate matter and discoloration prior to administration, whenever solution and container permit. If these conditions exist, the product should not be administered.

After removing the "flip-off" cap, cleanse the vaccine vial stopper with a suitable germicide. Do not remove either the rubber stopper or the metal seal holding it in place. Just before use, shake the vial well until a uniform, white, cloudy suspension results.

Using a sterile needle and syringe and aseptic technique, withdraw and administer a single 0.5 mL dose of Diphtheria and Tetanus Toxoids Adsorbed intramuscularly. Use a separate sterile needle and syringe for each injection. Changing needles between withdrawing the vaccine from the vial and injecting it into a recipient is not necessary unless the needle has been damaged or contaminated. In infants younger than 1 year, the anterolateral aspect of the thigh provides the largest muscle and is the preferred site of injection. In older children, the deltoid muscle is usually large enough for injection. The vaccine should not be injected into the gluteal area or areas where there may be a major nerve trunk.

Diphtheria and Tetanus Toxoids Adsorbed vaccine should not be combined through reconstitution or mixed with any other vaccine. Discard unused portion.

3 DOSAGE FORMS AND STRENGTHS

Diphtheria and Tetanus Toxoids Adsorbed is a suspension for injection in 0.5 mL single-dose vials.

4 CONTRAINDICATIONS

A severe allergic reaction (e.g., anaphylaxis) after a previous dose of Diphtheria and Tetanus Toxoids Adsorbed or any other diphtheria toxoid or tetanus toxoid-containing vaccine, or any other component of this vaccine is a contraindication to administration of Diphtheria and Tetanus Toxoids Adsorbed. [See Description (11).]

5 WARNINGS AND PRECAUTIONS

5.1 Management of Acute Allergic Reactions

Epinephrine Injection (1:1000) and other appropriate agents and equipment must be available for immediate use in case an anaphylactic or acute hypersensitivity reaction occurs.

5.2 Guillain-Barré Syndrome and Brachial Neuritis

A review by the Institute of Medicine (IOM) found evidence for a causal relation between tetanus toxoid and both brachial neuritis and Guillain-Barré syndrome. (1) If Guillain-Barré syndrome occurred within 6 weeks of receipt of prior vaccine containing tetanus toxoid, the risk for Guillain-Barré syndrome may be increased following Diphtheria and Tetanus Toxoids Adsorbed vaccine.

5.3 Limitation of Vaccine Effectiveness

Vaccination with Diphtheria and Tetanus Toxoids Adsorbed may not protect all individuals.

5.4 Altered Immunocompetence

If Diphtheria and Tetanus Toxoids Adsorbed vaccine is administered to immunocompromised persons, including persons receiving immunosuppressive therapy, the expected immune response may not be obtained. [See Immunosuppressive Treatments (7.3).]

5.5 Apnea in Premature Infants

Apnea following intramuscular vaccination has been observed in some infants born prematurely. The decision about when to administer an intramuscular vaccine, including Diphtheria and Tetanus Toxoids Adsorbed, to an infant born prematurely should be based on consideration of the individual infant's medical status and the potential benefits and possible risks of vaccination.

5.6 Syncope

Syncope (fainting) has been reported following vaccination with Diphtheria and Tetanus Toxoids Adsorbed vaccine. Procedures should be in place to prevent falling injury and manage syncopal reactions.

6 ADVERSE REACTIONS

The most common adverse reactions (≥5%) were crying, fever, and loss of appetite.

6.1 Clinical Trials Experience

Because clinical trials are conducted under widely varying conditions, adverse reaction rates observed in the clinical trials of a vaccine cannot be directly compared to rates in the clinical trials of another vaccine and may not reflect the rates observed in practice. The adverse reaction information from clinical trials does, however, provide a basis for identifying the adverse events that appear to be related to vaccine use and for approximating rates of those events.

In a clinical trial in Baltimore, 163 infants received Diphtheria and Tetanus Toxoids Adsorbed at 2, 4 and 6 months of age. The results of this trial are presented in Table 1.

Table 1: Percentage of Children Experiencing Local and Systemic Reactions at 24 Hours Following Immunization
Reaction | BALTIMORE [A total of 163 children received one of the three lots of Diphtheria and Tetanus Toxoids Adsorbed at 2, 4, and 6 months of age, and acellular pertussis vaccine at 3, 5, and 7 months of age. One control group (N=85) received Diphtheria and Tetanus Toxoids Adsorbed concurrently at a separate site with acellular pertussis vaccine at 2, 4 and 6 months of age (data not shown). A second control group (N=85) received commercial DTwP vaccine at 2, 4, and 6 months of age, and a placebo at 3, 5, and 7 months of age (data not shown).] (N=163)
Reaction | Dose 1 (%) (n = 155) | Dose 2 (%) (n = 145) | Dose 3 (%) (n = 136)
Systemic Reactions
Fever ≥38°C <39°C (≥100.4°F <102.2°F) | 0.7 | 0.8 | 6.6
Fever ≥39°C (≥102.2°F) | 0 | 0 | 0
Crying | 13.6 | 15.2 | 13.0
Loss of Appetite | 3.9 | 6.2 | 2.9
Injection Site Reactions
Redness ≥2.5 cm | 0.7 | 0 | 3.6
Slight Pain | 2.6 | 2.8 | 2.2
Moderate Pain | 0.7 | 1.4 | 0
Hardness ≥2.5 cm | 1.3 | 1.4 | 3.6

Two clinical trials were conducted in Canada. In the first clinical trial, 52 children aged 17-22 months who had previously received 3 doses of whole-cell DTP Adsorbed vaccine (not licensed in US), received Diphtheria and Tetanus Toxoids Adsorbed with either an acellular pertussis (n = 25) or a whole cell pertussis (n = 27) vaccine (neither licensed in US) given concurrently but at a separate site. The only reported local reaction was slight pain at the Diphtheria and Tetanus Toxoids Adsorbed injection site in 11% of children.

In a second clinical trial conducted in Canada, 99 children aged 4 to 6 years old who were eligible for the preschool (fifth) dose of DTP received Diphtheria and Tetanus Toxoids Adsorbed in one arm and a whole-cell Monovalent Pertussis vaccine (not licensed in US) in the other. The following local reactions at the Diphtheria and Tetanus Toxoids Adsorbed injection site were reported: redness ≥50 mm - 9%, swelling >50 mm - 51%, tenderness, moderate or severe - 17%, arm mobility "too sore to move" - 9%. (2)

Diphtheria and Tetanus Toxoids Adsorbed evaluated in clinical trials contained thimerosal.

6.2 Postmarketing Experience

The following adverse events have been spontaneously reported during the postmarketing use of a Diphtheria and Tetanus Toxoids Adsorbed vaccine manufactured by Sanofi Pasteur Limited that contained thimerosal. Because these events are reported voluntarily from a population of uncertain size, it is not always possible to reliably estimate their frequency or establish a causal relationship to vaccine exposure.

The following adverse events were included based on severity, frequency of reporting or the strength of causal association with Diphtheria and Tetanus Toxoids Adsorbed:

Blood and lymphatic system disorders

Lymphadenopathy

Gastrointestinal disorders

Nausea

General disorders and administration site conditions

Injection site inflammation
Injection site hypersensitivity
Pain

Nervous system disorders

Convulsion
Somnolence
Syncope
Headache

Skin and subcutaneous tissue disorders

Rash
Urticaria

Vascular disorders

Pallor

7 DRUG INTERACTIONS

7.1 Concomitant Administration with Other Vaccines

No safety and immunogenicity data are available on the concomitant administration of Diphtheria and Tetanus Toxoids Adsorbed with other US licensed vaccines.

7.2 Concomitant Administration with Tetanus Immune Globulin (Human)

If passive protection against tetanus is required, TIG (Human) may be administered according to its prescribing information, concomitantly with Diphtheria and Tetanus Toxoids Adsorbed at a separate site with a separate needle and syringe.

7.3 Immunosuppressive Treatments

Immunosuppressive therapies, including irradiation, antimetabolites, alkylating agents, cytotoxic drugs and corticosteroids (used in greater than physiologic doses), may reduce the immune response to Diphtheria and Tetanus Toxoids Adsorbed. [See Warnings and Precautions (5.4).]

8 USE IN SPECIFIC POPULATIONS

8.1 Pregnancy

Diphtheria and Tetanus Toxoids Adsorbed is not approved for use in individuals 7 years of age and older. Human or animal data are not available to assess vaccine-associated risks in pregnancy.

8.2 Lactation

Diphtheria and Tetanus Toxoids Adsorbed is not approved for use in individuals 7 years of age and older. Human or animal data are not available to assess the impact of Diphtheria and Tetanus Toxoids Adsorbed on milk production, its presence in breast milk, or its effects on the breastfed infant.

8.4 Pediatric Use

Diphtheria and Tetanus Toxoids Adsorbed is not indicated for infants below 6 weeks of age or children 7 years of age or older. Safety and effectiveness of Diphtheria and Tetanus Toxoids Adsorbed in these age groups have not been established.

11 DESCRIPTION

Diphtheria and Tetanus Toxoids Adsorbed is a sterile, cloudy, white, uniform suspension of diphtheria and tetanus toxoids adsorbed on aluminum phosphate and suspended in isotonic sodium chloride solution for intramuscular injection only. Diphtheria and Tetanus Toxoids Adsorbed vaccine does not contain a preservative.

Each 0.5 mL dose is formulated to contain: 25 Lf diphtheria toxoid and 5 Lf tetanus toxoid. Other ingredients per 0.5 mL dose include: 1.5 mg aluminum phosphate and <100 mcg free formaldehyde.

Diphtheria toxoid is prepared from the toxin produced during the growth of a selected strain of Corynebacterium diphtheriae grown with aeration in submerged culture. The toxin is purified by precipitation, converted to toxoid by the addition of formalin and concentrated by ultrafiltration. The culture medium consists of a tryptic digest of casein, supplemented with cystine, maltose, uracil, inorganic salts and vitamins.

Tetanus toxoid is prepared from the toxin produced during the growth of a selected strain of Clostridium tetani. The toxin is converted to toxoid by the addition of formalin, concentrated and then purified. The culture medium consists of a tryptic digest of casein, supplemented with cystine, dextrose, uracil, inorganic salts and vitamins.

When tested in guinea pigs, the tetanus and diphtheria components induce at least 2 neutralizing units/mL of serum.

The vial stopper is not made with natural rubber latex.

12 CLINICAL PHARMACOLOGY

12.1 Mechanism of Action

Diphtheria is an acute toxin-mediated disease caused by toxigenic strains of C. diphtheriae. Protection against disease is due to the development of neutralizing antibodies to diphtheria toxin. A serum diphtheria antitoxin level of 0.01 International Units (IU)/mL is the lowest level giving some degree of protection, and levels of at least 0.1 IU/mL are generally regarded as protective. (3) (4)

Tetanus is an acute disease caused by an extremely potent neurotoxin produced by C. tetani. Protection against disease is due to the development of neutralizing antibodies to tetanus toxin. A serum tetanus antitoxin level of 0.01 IU/mL, measured by neutralization assay is considered the minimum protective level. (3) (5)

13 NONCLINICAL TOXICOLOGY

13.1 Carcinogenesis, Mutagenesis, Impairment of Fertility

Diphtheria and Tetanus Toxoids Adsorbed has not been evaluated for carcinogenicity, mutagenic potential, or impairment of fertility.

14 CLINICAL STUDIES

In a clinical study conducted in Baltimore, MD, infants received one of three lots of Diphtheria and Tetanus Toxoids Adsorbed (formulation that contained thimerosal), 0.5 mL, at 2, 4 and 6 months of age. Oral poliovirus vaccine (no longer licensed in the US) was administered concomitantly with Diphtheria and Tetanus Toxoids Adsorbed at 2 and 4 months of age. Diphtheria and tetanus antitoxin levels were evaluated at 8 months of age (see Table 2). Protective levels of diphtheria antitoxin (≥0.01 IU/mL) and tetanus antitoxin (≥0.01 IU/mL) were detected in 99% and 100%, respectively, of the Diphtheria and Tetanus Toxoids Adsorbed recipients after 3 doses. The geometric mean titers (GMT's) for diphtheria and tetanus antitoxin antibodies in recipients of the three Diphtheria and Tetanus Toxoids Adsorbed lots were not significantly different, ranging from 0.25 to 0.35 IU/mL for diphtheria antitoxin antibodies, and from 0.75 to 0.80 IU/mL for tetanus antibodies after the third dose. In a fourth group of 75 infants who received an investigational acellular pertussis vaccine simultaneously with the Diphtheria and Tetanus Toxoids Adsorbed but at separate sites with separate needles and syringes, protective diphtheria and tetanus antitoxin levels developed in 100% of the recipients.

Table 2: Percentage of Children Protected Following Administration of Diphtheria and Tetanus Toxoids Adsorbed
 | Post Dose 3 Diphtheria and Tetanus Toxoids Adsorbed
Diphtheria antitoxin ≥0.01 IU/mL | 99% (135/136)
Tetanus antitoxin ≥0.01 IU/mL | 100% (137/137)

15 REFERENCES

1 Adverse Events Associated with Childhood Vaccines. Institute of Medicine. 1994.
2 Scheifele D, et al. Role of whole-cell pertussis vaccine in severe local reactions to the preschool (fifth) dose of diphtheria-pertussis-tetanus vaccine. Can Med Assoc Journal 1994;150(1).
3 Department of Health and Human Services, Food and Drug Administration. Biological products; bacterial vaccines and toxoids; implementation of efficacy review; proposed rule. Federal Register 1985;50(240):51002-117.
4 Vitek CR, Wharton M. Diphtheria toxoid. In: Plotkin SA, Orenstein WA, Offit PA, editors. Vaccines. 5th ed. Philadelphia, PA: W.B. Saunders; 2008. p. 139-56.
5 Wassilak SGF, et al. Tetanus toxoid. In: Plotkin SA, Orenstein WA, Offit PA, editors. Vaccines. 5th ed. Philadelphia, PA: W.B. Saunders; 2008. p. 805-39.

16 HOW SUPPLIED/STORAGE AND HANDLING

Diphtheria and Tetanus Toxoids Adsorbed is supplied in:
a 0.5 mL single-dose vial: NDC No. 49281-225-58;
in packages of 10 vials: NDC No. 49281-225-10.

The vial stopper is not made with natural rubber latex.

STORAGE AND HANDLING

Diphtheria and Tetanus Toxoids Adsorbed should be stored at 2° to 8°C (35° to 46° F). Do not freeze. Product which has been exposed to freezing should not be used. Do not use vaccine beyond the expiration date. Discard unused portion.

17 PATIENT COUNSELING INFORMATION

Inform the parent or guardian of the following:

- It is important to complete the immunization series for maximum protection against diphtheria and tetanus.
- Common adverse reactions include local redness, swelling, and tenderness at the injection site, fever, crying, and loss of appetite.
- Other adverse reactions can occur. Call your healthcare provider with any adverse reactions of concern.
- Provide the Vaccine Information Statements (VIS), which are required by the National Childhood Vaccine Injury Act of 1986.

Manufactured by:
Sanofi Pasteur Limited
Toronto Ontario Canada

Distributed by:
Sanofi Pasteur Inc.
Swiftwater PA 18370 USA

R7-0319 USA

PRINCIPAL DISPLAY PANEL - 0.5 mL Vial Label

NDC 49281-225-58
DT

Diphtheria
and Tetanus
Toxoids
Adsorbed

Rx only

For 6 wks - 6 yrs of age

Single-dose (0.5 mL) IM only

Sanofi Pasteur Limited

PRINCIPAL DISPLAY PANEL - 10 Vial Package

NDC 49281-225-10
DT

Diphtheria and
Tetanus Toxoids
Adsorbed

For children 6 weeks
through 6 years of age

10
single-
dose
vials

Rx only

SANOFI PASTEUR